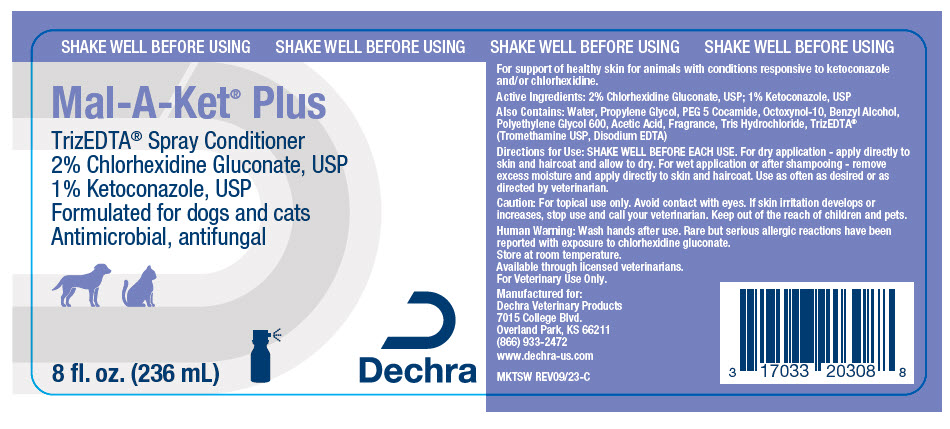 DRUG LABEL: MAL-A-KET PLUS 
NDC: 17033-203 | Form: SPRAY
Manufacturer: Dechra Veterinary Products
Category: animal | Type: OTC ANIMAL DRUG LABEL
Date: 20231114

ACTIVE INGREDIENTS: CHLORHEXIDINE GLUCONATE 2 g/100 mL; KETOCONAZOLE 1 g/100 mL

Mal-A-Ket® + TrizEDTA® Spray Conditioner

VETERINARY INDICATIONS

For support of healthy skin for animals with conditions responsive to ketoconazole and/or chlorhexidine.

DESCRIPTION

Active Ingredients: 2% Chlorhexidine Gluconate, USP; 1% Ketoconazole, USP

Also Contains: Water, Propylene Glycol, PEG 5 Cocamide, Octoxynol-10, Benzyl Alcohol, Polyethylene Glycol 600, Acetic Acid, Fragrance, Tris Hydrochloride, TrizEDTA® (Tromethamine USP, Disodium EDTA)

DOSAGE AND ADMINISTRATION

Directions for Use: SHAKE WELL BEFORE EACH USE. For dry application - apply directly to skin and haircoat and allow to dry. For wet application or after shampooing - remove excess moisture and apply directly to skin and haircoat. Use as often as desired or as directed by veterinarian.

SAFE HANDLING WARNING

Caution: For topical use only. Avoid contact with eyes. If skin irritation develops or increases, stop use and call your veterinarian. Keep out of the reach of children and pets.

WARNINGS

Human Warning: Wash hands after use. Rare but serious allergic reactions have been reported with exposure to chlorhexidine gluconate.

STORAGE AND HANDLING

Store at room temperature.

Available through licensed veterinarians.

For Veterinary Use Only.

Manufactured for:
Dechra Veterinary Products
7015 College Blvd.
Overland Park, KS 66211
(866) 933-2472
www.dechra-us.com

MKTSW REV09/23-C

PRINCIPAL DISPLAY PANEL - 236 mL Bottle Label

SHAKE WELL BEFORE USING

Mal-A-Ket® Plus

TrizEDTA® Spray Conditioner
2% Chlorhexidine Gluconate, USP
1% Ketoconazole, USP
Formulated for dogs and cats
Antimicrobial, antifungal

8 fl. oz. (236 mL)

Dechra